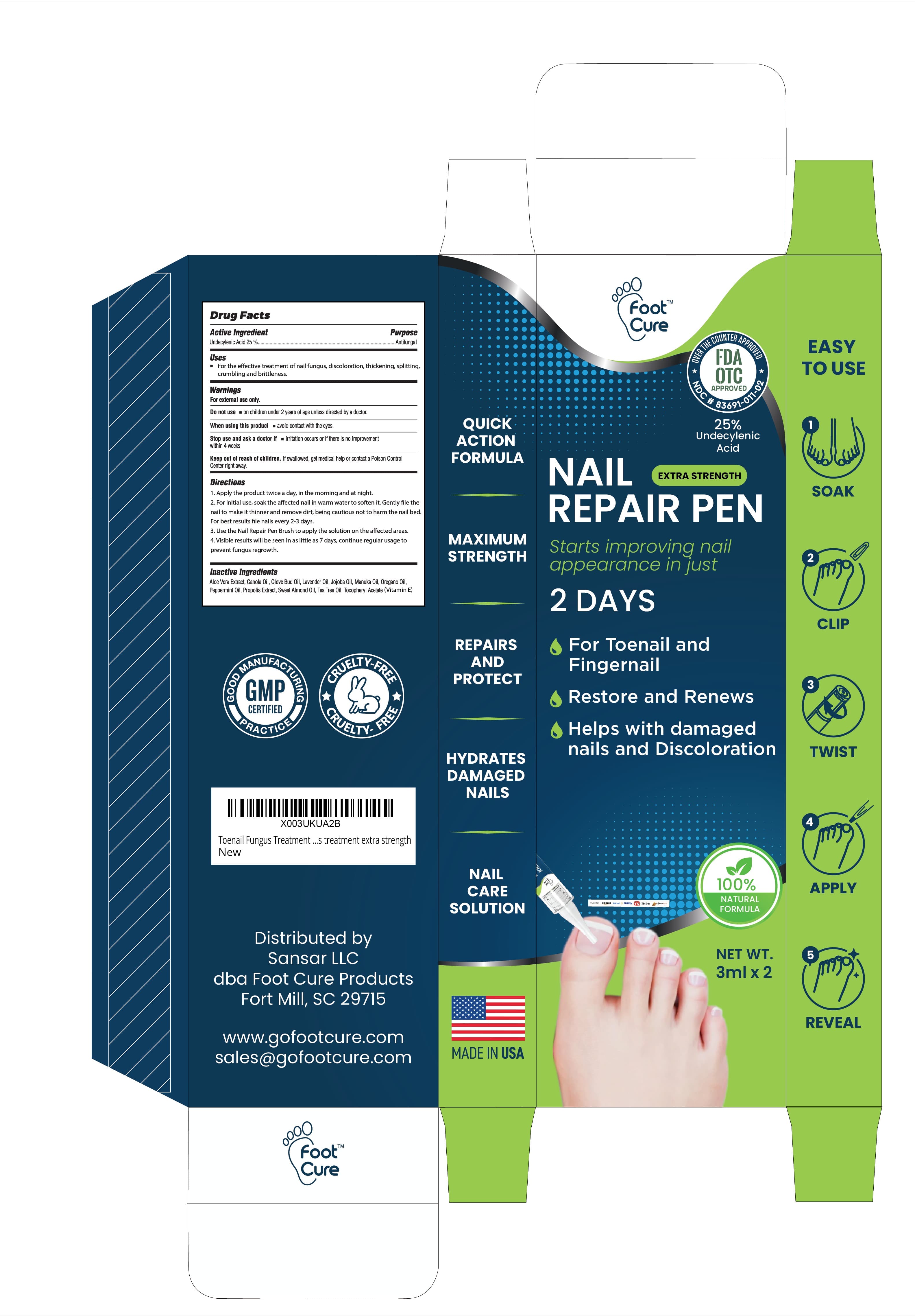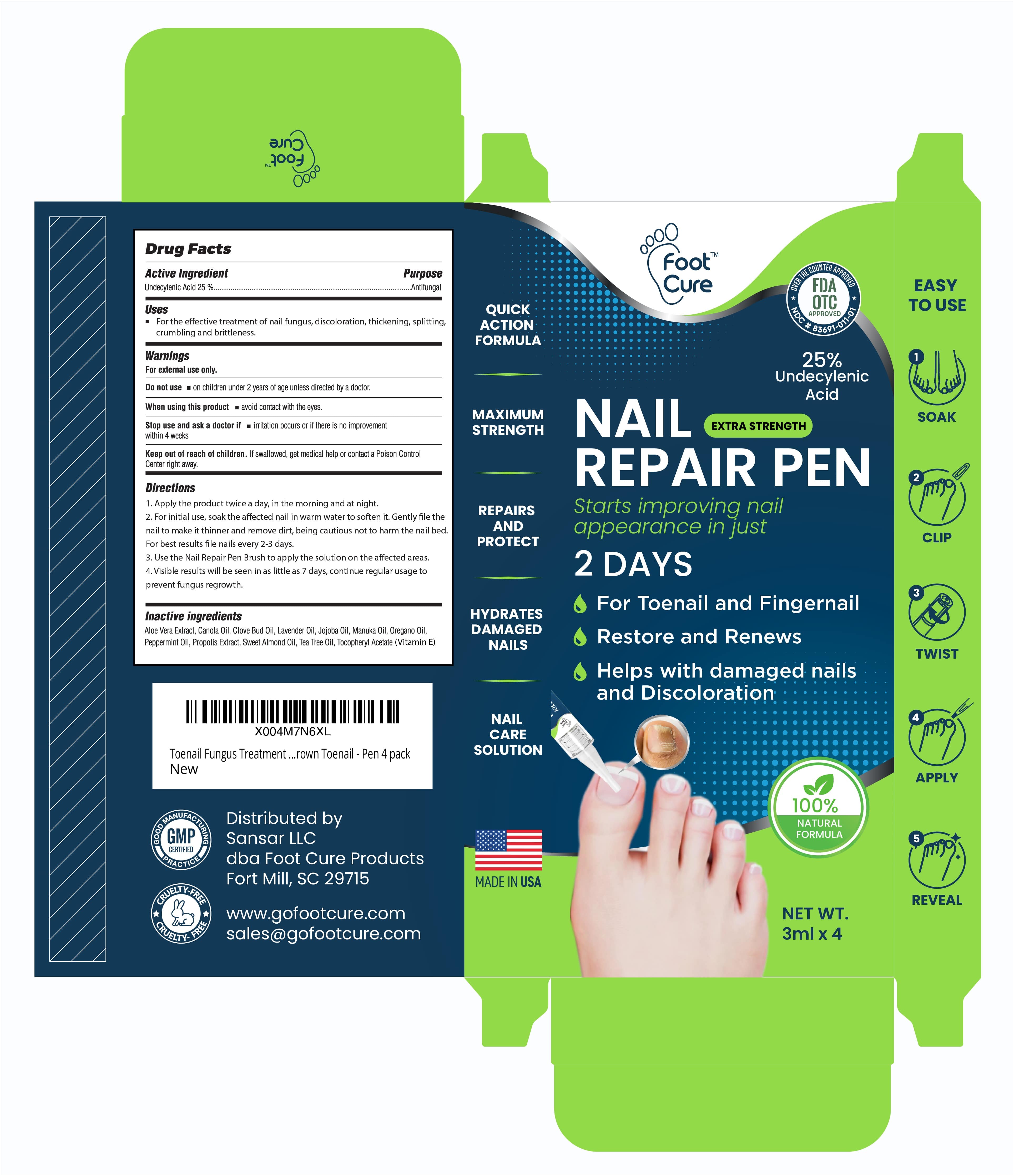 DRUG LABEL: Foot Cure Nail Repair Pen
NDC: 83691-011 | Form: SOLUTION
Manufacturer: SANSAR, LLC
Category: otc | Type: HUMAN OTC DRUG LABEL
Date: 20250425

ACTIVE INGREDIENTS: UNDECYLENIC ACID 25 g/100 mL
INACTIVE INGREDIENTS: ALOE VERA LEAF; CANOLA OIL; CLOVE OIL; LAVENDER OIL; JOJOBA OIL; MANUKA OIL; OREGANO LEAF OIL; PEPPERMINT OIL; PROPOLIS WAX; ALMOND OIL; TEA TREE OIL; .ALPHA.-TOCOPHEROL

Active ingredient

Undecylenic Acid 25%

Purpose

Antifungal

Uses

For the Effective treatment of nail fungus, discoloration, thickening, splitting, crumbling and britteleness

Warnings

For external use only.

Do not use

- on children under 2 years of age unless directed by a doctor.

When using this product

- avoid contact with eyes.

Stop use and ask a doctor if

- irritation occurs or there is no improvement within 4 weeks.

Keep out of reach of children. If swallowed, get medical help or contact a Poison Control Center right away.

Directions

1. Apply the product twice a day, in the morning and at night.

2. For initial use, soak the affected nail in warm water to soften it. Gently file the nail to make it thinner and remove dirt, being cautios not to harm the nail bed. For best results file nails every 2-3 days.

3. Use the Nail Repair pen brush to apply the solution on the affected areas.

4. Visible results will be seen in as little as 7 days, continue regular usage to prevent fungus regrowth.

Inactive Ingredients

Aloe Vera Extract, Canola Oil, Clove bud oil, Lavender oil, Jojoba Oil, Manuka Oil, Oregano Oil, Peppermint Oil, Propolis Extract, Sweet Almond oil, Tea tree oil, Tocopheryl Acetate (Vitamin E)